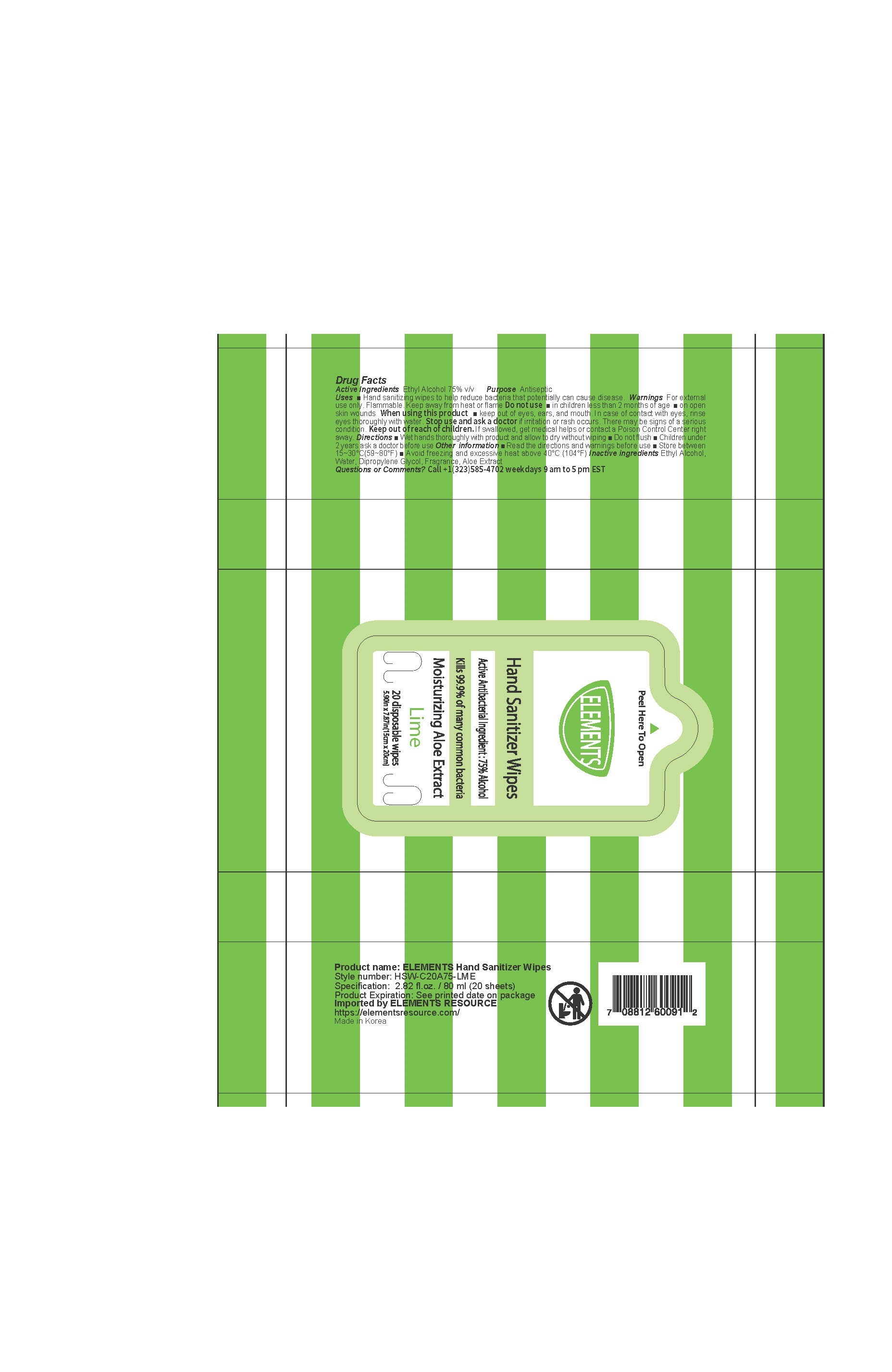 DRUG LABEL: ELEMENTS ETHANOL 75% HAND SANITIZER WIPES
NDC: 74200-0031 | Form: LIQUID
Manufacturer: URBANBCL CO LTD
Category: otc | Type: HUMAN OTC DRUG LABEL
Date: 20200720

ACTIVE INGREDIENTS: ALCOHOL 75 mL/100 g
INACTIVE INGREDIENTS: WATER; ALOE VERA LEAF; DIPROPYLENE GLYCOL

Drug Facts

ACTIVE INGREDIENT

ethyl alcohol

PURPOSE

Hand sanitizing wipes to help reduce bacteria that potentially can cause disease

KEEP OUT OF REACH OF THE CHILDREN

WARNINGS

■ Flammable. Keep away from fire or flame.

■ For external use only.

■ Do not use in eyes.

■ lf swallowed, get medical help promptly.

■ Stop use, ask doctor lf irritation occurs.

■ Keep out of reach of children.

DOSAGE AND ADMINISTRATION

for external use only

INACTIVE INGREDIENT

Water, Dipropylene Glycol, Fragrance, Aloe Extract

INDICATIONS AND USAGE

■ Wet hands thoroughly with product and allow to dry without wiping

■ Do not flush

■ Children under 2 years ask a doctor before use